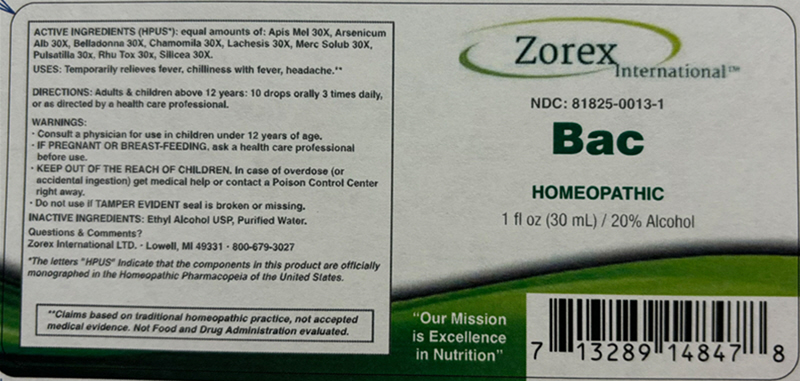 DRUG LABEL: Bac
NDC: 81825-0013 | Form: LIQUID
Manufacturer: Zorex
Category: homeopathic | Type: HUMAN OTC DRUG LABEL
Date: 20250630

ACTIVE INGREDIENTS: APIS MELLIFERA 30 [hp_X]/1 mL; ARSENIC TRIOXIDE 30 [hp_X]/1 mL; ATROPA BELLADONNA 30 [hp_X]/1 mL; MATRICARIA CHAMOMILLA FLOWERING TOP OIL 30 [hp_X]/1 mL; LACHESIS MUTA VENOM 30 [hp_X]/1 mL; MERCURIUS SOLUBILIS 30 [hp_X]/1 mL; PULSATILLA VULGARIS WHOLE 30 [hp_X]/1 mL; TOXICODENDRON PUBESCENS LEAF 30 [hp_X]/1 mL; SILICON DIOXIDE 30 [hp_X]/1 mL
INACTIVE INGREDIENTS: Alcohol; Water

Bac

Drug Facts

ACTIVE INGREDIENT (HPUS [The letters "HPUS" indicate that the components in this product are officially monographed in the Homeopathic Pharmacopeia of the United States.])

equal amounts of: Apis Mel 30X, Arsenicum Alb 30X, Belladonna 30X, Chamomilla 30X, Lachesis 30X, Merc Solub 30X, Pulsatilla 30X, Rhus Tox 30X, Silicea 30X.

USES

PURPOSE

Temporarily relieves fever, chilliness with fever, headache. [Claims based on traditional homeopathic practice, not accepted medical evidence. Not Food and Drug Administration evaluated.]

DIRECTIONS

Adults & children above 12 years: 10 drops orally 3 times daily, or as directed by a health care professional.

WARNINGS

PREGNANCY OR BREAST FEEDING

- Consult a physician for use in children under the age 12 years of age.
- IF PREGNANT OR BREAST-FEEDING, ask a health care professional before use.

KEEP OUT OF REACH OF CHILDREN

- KEEP OUT OF THE REACH OF CHILDREN. In case of overdose (or accidental ingestion) get medical help or contact Poison Control Center right away.

- Do not use if TAMPER EVIDENT seal is broken or missing.

INACTIVE INGREDIENTS

Ethyl Alcohol USP, Purified Water.

Questions & Comments?

Zorex International LTD. ∙ Lowell, MI 40331 ∙ 800-670-3027

PRINCIPAL DISPLAY PANEL - 30 mL Bottle Label

Zorex
International™

NDC: 81825-0013-1

Bac

HOMEOPATHIC
1 fl oz (30 mL) / 20% Alcohol

"Our Mission
is Excellence
in Nutrition"